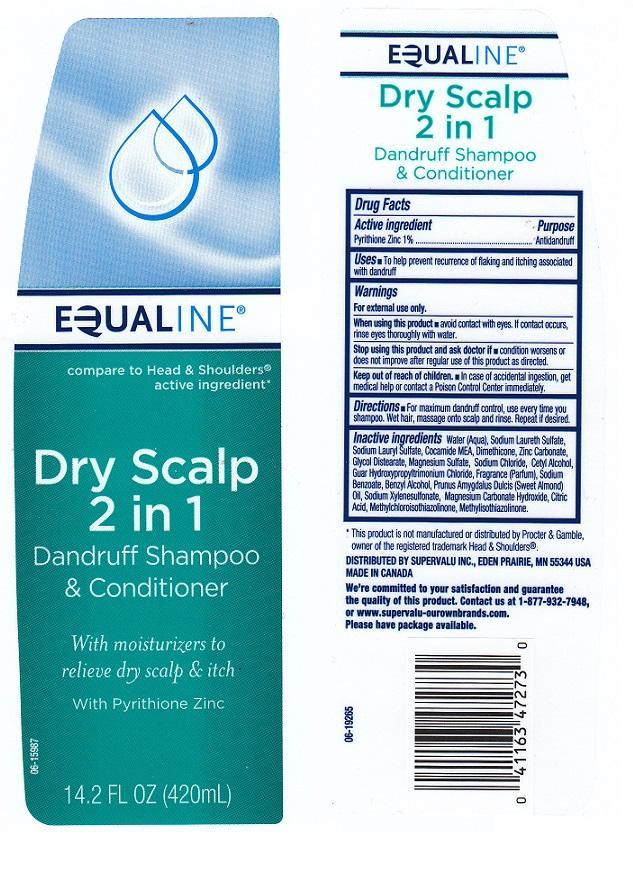 DRUG LABEL: EQUALINE
NDC: 41163-425 | Form: LIQUID
Manufacturer: SUPERVALU INC
Category: otc | Type: HUMAN OTC DRUG LABEL
Date: 20140801

ACTIVE INGREDIENTS: PYRITHIONE ZINC 10 mg/1 mL
INACTIVE INGREDIENTS: WATER; SODIUM LAURETH SULFATE; SODIUM LAURYL SULFATE; COCO MONOETHANOLAMIDE; DIMETHICONE; ZINC CARBONATE; GLYCOL DISTEARATE; MAGNESIUM SULFATE; SODIUM CHLORIDE; CETYL ALCOHOL; GUAR HYDROXYPROPYLTRIMONIUM CHLORIDE (1.7 SUBSTITUENTS PER SACCHARIDE); SODIUM BENZOATE; BENZYL ALCOHOL; ALMOND OIL; SODIUM XYLENESULFONATE; MAGNESIUM CARBONATE HYDROXIDE; CITRIC ACID MONOHYDRATE; METHYLCHLOROISOTHIAZOLINONE; METHYLISOTHIAZOLINONE

DRUG FACTS

ACTIVE INGREDIENT

PYRITHIONE ZINC 1%

PURPOSE

ANTIDANDRUFF

INDICATIONS AND USAGE

TO HELP PREVENT RECURRENCE OF FLAKING AND ITCHING ASSOCIATED WITH DANDRUFF

WARNINGS

FOR EXTERNAL USE ONLY

WHEN USING THIS PRODUCT

AVOID CONTACT WITH EYES. IF CONTACT OCCURS, RINSE EYES THOROUGHLY WITH WATER

STOP USING THIS PRODUCT AND ASK DOCTOR IF

CONDITION WORSENS OR DOES NOT IMPROVE AFTER REGULAR USE OF THIS PRODUCT AS DIRECTED

KEEP OUT OF REACH OF CHILDREN

IN CASE OF ACCIDENTAL INGESTION, GET MEDICAL HELP OR CONTACT A POISON CONTROL CENTER IMMEDIATELY

DIRECTIONS

FOR MAXIMUM DANDRUFF CONTROL, USE EVERY TIME YOU SHAMPOO. WET HAIR, MASSAGE ONTO SCALP AND RINSE. REPEAT IF DESIRED

INACTIVE INGREDIENTS

WATER (AQUA), SODIUM LAURETH SULFATE, SODIUM LAURYL SULFATE, COCAMIDE MEA, DIMETHICONE, ZINC CARBONATE, GLYCOL DISTEARATE, MAGNESIUM SULFATE, SODIUM CHLORIDE, CETYL ALCOHOL, GUAR HYDROXYPROPYLTRIMONIUM CHLORIDE, FRAGRANCE (PARFUM), SODIUM BENZOATE, BENZYL ALCOHOL, PRUNUS AMYGDALUS DULCIS (SWEET ALMOND) OIL, SOIDUM XYLENESULFONATE, MAGNESIUM CARBONATE HYDROXIDE, CITRIC ACID, METHYLCHLOROISOTHIAZOLINONE, METHYLISOTHIAZOLINONE